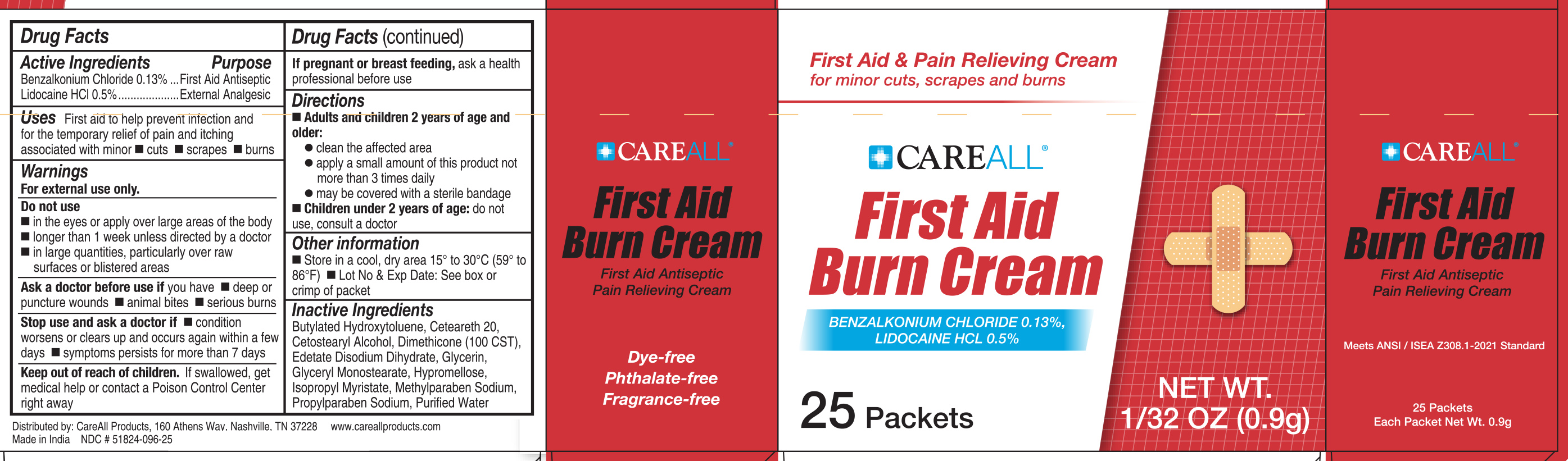 DRUG LABEL: CareALL First Aid Burn Cream
NDC: 51824-096 | Form: CREAM
Manufacturer: New World Imports, Inc
Category: otc | Type: HUMAN OTC DRUG LABEL
Date: 20251222

ACTIVE INGREDIENTS: BENZALKONIUM CHLORIDE 0.005 g/1 g; LIDOCAINE HYDROCHLORIDE 0.0013 g/1 g
INACTIVE INGREDIENTS: BUTYLATED HYDROXYTOLUENE; POLYOXYL 20 CETOSTEARYL ETHER; CETOSTEARYL ALCOHOL; DIMETHICONE 100; EDETATE DISODIUM; GLYCERIN; GLYCERYL MONOSTEARATE; HYPROMELLOSE, UNSPECIFIED; ISOPROPYL MYRISTATE; METHYLPARABEN SODIUM; PROPYLPARABEN SODIUM; WATER

Active Ingredients

Benzalkonium Chloride 0.13%

Lidocaine HCl 0.5%

Purpose

Benzalkonium Chloride 0.13%.....First Aid Antiseptic

Lidocaine HCl 0.5%....................External Analgesic

Keep out of reach of children. If swallowed, get medical help or contact a poison control center right away

Uses

First aid to help prevent infection and for the temporary relief of pain and itching associated with minor cuts, scrapes and burns

Warnings

For external use only.

Do not use:

- in the eyes or apply over large areas of the body
- longer than 1 week unless directed by a doctor
- in large quantities, particularly over raw surfaces or blistered areas

Ask a doctor before use if you have:

- deep or puncture wounds
- animal bites
- serious burns

Stop use and ask a doctor if:

- condition worsens or clears up and occurs again within a few days
- symptoms persists for more than 7 days

Pregnant or breast feeding

If pregnant or breast feeding, ask a health professional before use

Directions

Adults and children 2 years of age and older:

- clean the affected area
- apply a small amount of this product not more than 3 times daily
- may be covered with sterily bandage

Children under 2 years of age:do not use, consult a doctor

Inactive Ingredients

Butylated Hydroxytoluene, Ceteareth 20, Cetostearyl Alcohol, Dimethicone (100 CST), Edetate Disodium Dihydrate, Glycerin, Glyceryl Monostearate, Hypromellose, Isopropyl Myristate, Methylparaben Sodium, Propylparaben Sodium, Purified Water